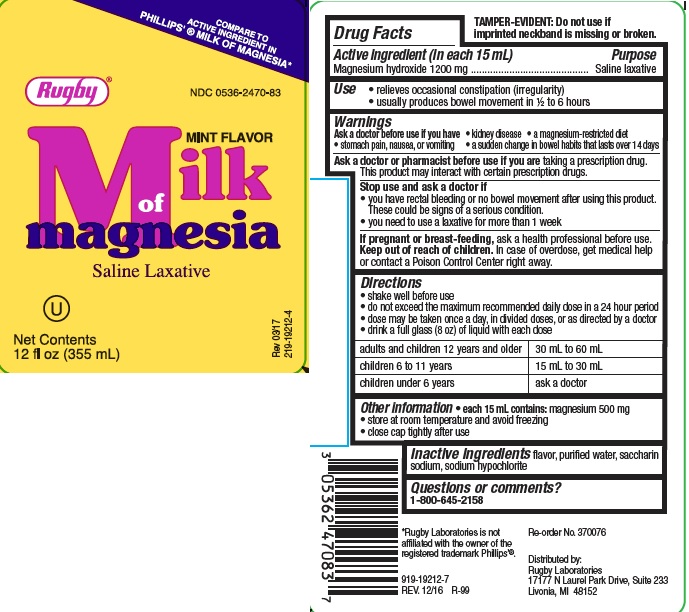 DRUG LABEL: MILK OF MAGNESIA MINT
NDC: 0536-2470 | Form: LIQUID
Manufacturer: Rugby Laboratories
Category: otc | Type: HUMAN OTC DRUG LABEL
Date: 20260209

ACTIVE INGREDIENTS: MAGNESIUM HYDROXIDE 1200 mg/15 mL
INACTIVE INGREDIENTS: WATER; SODIUM HYPOCHLORITE; SACCHARIN SODIUM

RUGBY MOM MINT

Active ingredient (in each 15 mL)

Magnesium hydroxide 1200 mg

Purpose

Saline laxative

Uses

- relieves occasional constipation (irregularity)
- usually produces bowel movement in 1/2 to 6 hours

Warnings

Ask a doctor before use if you have

- kidney disease
- a magnesium-restricted diet
- stomach pain, nausea, or vomiting
- a sudden change in bowel habits that lasts over 14 days

Ask a doctor or pharmacist before use if you are

taking a prescription drug.

This product may interact with certain prescription drugs.

Stop use and ask a doctor if

- you have rectal bleeding or no bowel movement after using this product. These could be signs of a serious condition.
- you need to use a laxative for more than 1 week

If pregnant or breast-feeding, ask a health professional before use.

Keep out of reach of children. In case of overdose, get medical help or contact a Poison Control Center right away.

Directions

- shake well before use
- do not exceed the maximum recommended daily dose in a 24 hour period
- dose may be taken once a day, in divided doses, or as directed by a doctor
- drink a full glass (8 oz) of liquid with each dose

adults and children 12 years and older | 30 mL to 60 mL
children 6 to 11 years | 15 mL to 30 mL
children under 6 years | ask a doctor

Other information

- each 15 mL contains: magnesium 500 mg
- store at room temperature and avoid freezing
- close cap tightly after use

Inactive ingredients

flavor, purified water, saccharin sodium, sodium hypochlorite

package Label

compare to active ingredient in phillips' milk of magnesia

Rugby

NDC 0536-2470-83
mint flavor

Milk of Magnesia

Saline Laxative

Net Contents
12 FL OZ (355 mL)